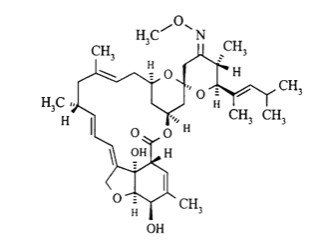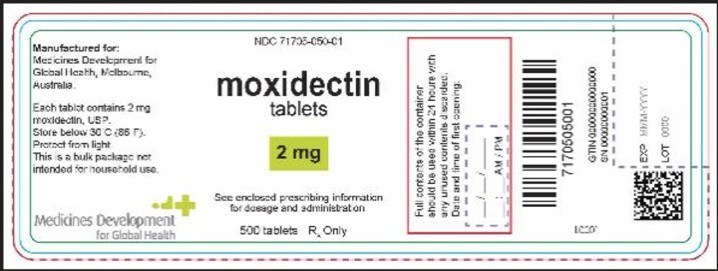 DRUG LABEL: Moxidectin
NDC: 71705-050 | Form: TABLET
Manufacturer: Medicines Development for Global Health
Category: prescription | Type: HUMAN PRESCRIPTION DRUG LABEL
Date: 20251013

ACTIVE INGREDIENTS: MOXIDECTIN 2 mg/1 1
INACTIVE INGREDIENTS: SILICON DIOXIDE; CROSCARMELLOSE SODIUM; ANHYDROUS LACTOSE; MAGNESIUM STEARATE; MICROCRYSTALLINE CELLULOSE; SODIUM LAURYL SULFATE

HIGHLIGHTS OF PRESCRIBING INFORMATION

MOXIDECTIN tablets, for oral use
These highlights do not include all the information needed to use MOXIDECTIN safely and effectively. See full prescribing information for MOXIDECTIN TABLETS.
Initial U.S. Approval: 2018

RECENT MAJOR CHANGES

Indications and Usage (1) 2/2025

Dosage and Administration (2.1,2.2) 2/2025

1 INDICATIONS AND USAGE

Moxidectin is an anthelmintic indicated for the treatment of onchocerciasis due to Onchocerca volvulus in adults and pediatric patients aged 4 years and older and weighing at least 13 kg. (1)

Limitations of Use:

- Moxidectin Tablets do not kill adult Onchocerca volvulus (O. volvulus)parasites. Follow-up is advised. (1)
- The safety and efficacy of repeat administration of Moxidectin Tablets in patients with O. volvulushas not been studied. (1)

2 DOSAGE AND ADMINISTRATION

- Recommended Dosage in Adult Patients: Take 8 mg (four 2 mg tablets) as a single oral dose, with or without food. (2.1)
- Recommended Dosage in Pediatric Patients (4 Years of Age and Older and Weighing at Least 13 kg):See Table below. (2.2)

Body Weight | Dose | Number of 2 mg Tablets
13 kg to less than 15 kg | 4 mg | 2
15 kg to less than 30 kg | 6 mg | 3
Greater than or equal to 30 kg | 8 mg | 4

3 DOSAGE FORMS AND STRENGTHS

Tablets: 2 mg of moxidectin. (3)

4 CONTRAINDICATIONS

None. (4)

5 WARNINGS AND PRECAUTIONS

- Cutaneous, Ophthalmologicaland/or Systemic Adverse Reactionsof Varying Severity (Mazzotti Reaction): This may occur in patients with onchocerciasis following treatment with Moxidectin Tablets. Monitor patients for symptoms, including symptomatic orthostatic hypotension. (5.1)
- Symptomatic Orthostatic Hypotension: Episodes of symptomatic orthostatic hypotension including inability to stand without support may occur in patients following treatment with Moxidectin Tablets. (5.2)
- Encephalopathy in Loa loa Co-Infected Patients: Serious or even fatal encephalopathy following treatment with Moxidectin Tablets may occur in patients co-infected with Loa loa. Assess patients for loiasis in Loa loaendemic areas prior to treatment. (5.3)
- Edema and Worsening of Onchodermatitis: Patients with hyper-reactive onchodermatitis (sowda) may be more likely than others to experience severe edema and aggravation of onchodermatitis. (5.4)

6 ADVERSE REACTIONS

- The most common adverse reactions (incidence > 10%) in adult and pediatric patients (12 to less than 18 years of age) in Trial 1 were eosinophilia, pruritus, musculoskeletal pain, headache, lymphocytopenia, tachycardia, rash, abdominal pain, hypotension, pyrexia, leukocytosis, influenza-like illness, neutropenia, cough, diarrhea/gastroenteritis/enteritis, lymph node pain, dizziness, hyponatremia and peripheral swelling. (6.1)
- The most common adverse reactions (incidence > 5%) in pediatric patients (4 to less than 18 years of age) in Trial 3 were abdominal pain and diarrhea. (6.1)

To report SUSPECTED ADVERSE REACTIONS, contact Medicines Development for Global Health at 1-800-MDGH-456 or FDA at 1-800-FDA-1088 or www.fda.gov/medwatch.

8 USE IN SPECIFIC POPULATIONS

Lactation: Breastfeeding is not recommended during treatment with Moxidectin Tablets and for 7 days after treatment. (8.2)

FULL PRESCRIBING INFORMATION

1 INDICATIONS AND USAGE

Moxidectin Tablets are indicated for the treatment of onchocerciasis due to Onchocerca volvulusin adult and pediatric patients aged 4 years and older and weighing at least 13 kg [see Clinical Studies (14)].

Limitations of Use:

Moxidectin Tablets does not kill adult Onchocerca volvulus (O. volvulus) parasites . Follow-up evaluation is advised.

The safety and efficacy of repeat administration of Moxidectin Tablets in patients with O. volvulushas not been studied.

2 DOSAGE AND ADMINISTRATION

2.1 Recommended Dosage in Adult Patients

The recommended dosage of Moxidectin Tablets in adult patients is a single dose of 8 mg (four 2 mg tablets) taken orally with or without food [see Clinical Pharmacology (12.3)].

2.2 Recommended Dosage in Pediatric Patients (4 Years of Age and Older and Weighing at Least 13 kg)

The recommended dosage of Moxidectin Tablets in pediatric patients aged 4 years and older and weighing at least 13 kg is described in Table 1 below. Administer Moxidectin Tablets as a single dose taken orally with or without food [see Clinical Pharmacology (12.3)].

Table 1: Recommended Dosage of Moxidectin Tablets in Pediatric Patients 4 Years of Age and Older and Weighing at Least 13 kg

Body Weight | Dose | Number of 2 mg Tablets
13 kg to less than 15 kg | 4 mg | 2
15 kg to less than 30 kg | 6 mg | 3
Greater than or equal to 30 kg | 8 mg | 4

3 DOSAGE FORMS AND STRENGTHS

Moxidectin Tablets: 2 mg of moxidectin, white to pale yellow, uncoated, oval-shaped, debossed on one side with “AKKA”.

4 CONTRAINDICATIONS

None.

5 WARNINGS AND PRECAUTIONS

5.1 Cutaneous, Ophthalmological and/or Systemic Adverse Reactions

Treatment with Moxidectin Tablets may cause cutaneous, ophthalmological and/or systemic reactions of varying severity (Mazzotti reaction). These adverse reactions are due to allergic and inflammatory host responses to the death of microfilariae [see Adverse Reactions (6.1)].There is a trend toward an increased incidence of these adverse reactions in patients with higher microfilarial burden.

The clinical manifestations of Mazzotti reaction include pruritus, headache, pyrexia, rash, urticaria, hypotension (including symptomatic orthostatic hypotension and dizziness) [ see Warnings and Precautions (5.2)], tachycardia, edema, lymphadenopathy, arthralgia, myalgia, chills, paresthesia and asthenia. Ophthalmological manifestations include conjunctivitis, eye pain, eye pruritus, eyelid swelling, blurred vision, photophobia, changes in visual acuity, hyperemia, ocular discomfort and watery eyes. These adverse reactions generally occur and resolve in the first week post-treatment. Laboratory changes include eosinophilia, eosinopenia, lymphocytopenia, neutropenia, and increases in alanine aminotransferase (ALT), aspartate aminotransferase (AST), gamma glutamyl transferase (GGT) and lactate dehydrogenase (LDH). Proteinuria has also been reported.

Treatment of severe Mazzotti reactions has not been evaluated in controlled clinical trials. Symptomatic treatments such as oral hydration, recumbency, intravenous normal saline, and/or parenteral corticosteroids have been used to treat orthostatic hypotension. Antihistamines and/or analgesics have been used for most mild to moderate cases.

5.2 Symptomatic Orthostatic Hypotension

An increased number of patients who received Moxidectin Tablets developed symptomatic orthostatic hypotension with inability to stand without support after lying down for 5 minutes (in an orthostatic hypotension provocation test); 47/978 (5%) compared with 8/494 (2%) who received ivermectin. The decreases in blood pressure were transient, managed by resumption of recumbency and most commonly occurred on Days 1 and 2 post-treatment. Advise patients that if they feel dizzy or light-headed after taking Moxidectin Tablets, they should lie down until the symptoms resolve.

5.3 Encephalopathy in Loa loa Co-infected Patients

Patients with onchocerciasis who are also infected with Loa loamay develop a serious or even fatal encephalopathy following treatment with Moxidectin Tablets.

Moxidectin Tablets have not been studied in patients co-infected with Loa loa. Therefore, it is recommended that individuals who warrant treatment with Moxidectin Tablets and have had exposure to Loa loa-endemic areas undergo diagnostic screening for loiasis prior to treatment.

5.4 Edema and Worseningof Onchodermatitis

Patients with hyper-reactive onchodermatitis (sowda) may be more likely than others to experience severe edema and worsening of onchodermatitis following the use of Moxidectin Tablets. Symptomatic treatment has been used to manage patients who have experienced edema and worsening of onchodermatitis.

6 ADVERSE REACTIONS

The following clinically significant adverse reactions are described in greater detail in other labeling sections:

- Cutaneous, Ophthalmological and/or Systemic Adverse Reactions [see Warnings and Precautions (5.1)]
- Symptomatic Orthostatic Hypotension [see Warnings and Precautions (5.2)]
- Encephalopathy in Loa loa Co-infected Patients [see Warnings and Precautions (5.3)]
- Edema and Worsening of Onchodermatitis [see Warnings and Precautions (5.4)]

6.1 Clinical Trials Experience

Because clinical trials are conducted under varying controlled conditions, adverse reaction rates observed in one clinical trial cannot be directly compared to rates observed in the clinical trials of another drug and may not reflect the rates observed in clinical practice.

Clinical Trials Experience in Adults and Pediatric Patients (12 Years to Less than 18 Years of Age)

The safety of Moxidectin Tablets was evaluated in two randomized, double-blind, active-controlled studies in patients with confirmed onchocerciasis (Trial 1 and Trial 2) [see Clinical Studies (14)]. In Trial 1, 978 patients (including 53 pediatric patients aged 12 to less than 18 years) received Moxidectin Tablets as a single oral dose of 8 mg and 494 patients received ivermectin (including 24 pediatric patients aged 12 to less than 18 years) as a single oral dose of approximately 150 mcg/kg. In Trial 2, 127 patients aged 18 years or older received Moxidectin Tablets as a single oral dose ranging from 2 mg (this is not an approved dose) to 8 mg (38 received the recommended 8 mg dose) and 45 patients aged 18 years or older received ivermectin as a single oral dose of approximately 150 mcg/kg.

Most Common Adverse Reactions

No patients withdrew from either trial due to adverse reactions. Adverse Reactions reported in Trial 1 in > 10% of patients are summarized in Table 2. Most were related to physical, vital signs and laboratory changes associated with Mazzotti reaction [see Warnings and Precautions (5.1)].

Table 2: Adverse Reactions Occurring in > 10% of Moxidectin-treated Patients with Onchocerciasis in Trial 1
Adverse Reaction | Moxidectin N = 978 n (%) | Ivermectin N = 494 n (%)
Eosinophilia | 721 (74) | 390 (79)
Pruritus | 640 (65) | 268 (54)
Musculoskeletal paina | 623 (64) | 257 (52)
Headache | 566 (58) | 267 (54)
Lymphocytopenia* | 470 (48) | 215 (44)
Tachycardiab | 382 (39) | 148(30)
Orthostatic tachycardiac | 333 (34) | 130 (26)
Non-orthostatic tachycardiad | 179 (18) | 57 (12)
Rashe | 358 (37) | 103 (21)
Abdominal painf | 305 (31) | 173 (35)
Hypotensiong | 289 (30) | 125 (25)
Orthostatic hypotensionh | 212 (22) | 81 (16)
Pyrexia/Chills | 268 (27) | 88 (18)
Leukocytosis | 240 (25) | 125 (25)
Influenza like illness | 226 (23) | 102 (21)
Neutropenia** | 197 (20) | 112 (23)
Cough | 168 (17) | 88 (18)
Lymph node pain | 129 (13) | 28 (6)
Dizziness | 121 (12) | 44 (9)
Diarrhea/Gastroenteritis/Enteritis | 144 (15) | 84 (17)
Hyponatremia | 112 (12) | 65 (13)
Peripheral swelling | 107 (11) | 30 (6)

aIncludes “myalgia”, “arthralgia”, “musculoskeletal pain”, “pain” and “back pain”

bIncludes “orthostatic heart rate increased”, “postural orthostatic tachycardia syndrome”, “heart rate increased” and “sinus tachycardia”

cIncludes “orthostatic heart rate increased” and “postural orthostatic tachycardia syndrome”

dIncludes “heart rate increased”, “tachycardia”, and “sinus tachycardia”

eIncludes “rash,” “papular rash” and “urticaria”

fIncludes “abdominal pain”, “abdominal pain upper” and “abdominal pain lower”

gIncludes “orthostatic hypotension”, “blood pressure orthostatic decreased”, “blood pressure decreased”, “mean arterial pressure decreased”, “hypotension”

hIncludes “orthostatic hypotension”, and “blood pressure orthostatic decreased”

*Lymphocytopenia is defined as absolute lymphocyte count less than 1 x 10^9/L

**Neutropenia is defined as absolute neutrophil count less than 1 x 10^9/L

The most common adverse reactions in patients (N = 38) treated with 8 mg moxidectin in Trial 2 were similar to the adverse reactions noted in Trial 1 described in Table 2above.

Other Adverse Reactions Reported in Clinical Trials (Trial 1 and Trial 2)

The following adverse reactions occurred in less than 10% of subjects receiving Moxidectin Tablets in Trial 1:

Ocular Adverse Reactions:In Trial 1, the most common ocular adverse reactions (occurring in ≥ 0.5% of patients) is shown in Table 3.

Table 3: Ocular Adverse Reactions Occurring in ≥ 0.5% Moxidectin-treated Patients
Adverse Reaction | Moxidectin N = 978 n (%) | Ivermectin N = 494 n (%)
Eye pain | 78 (8) | 28 (6)
Eye pruritus | 64 (7) | 26 (5)
Visual impairment* | 25 (3) | 9 (2)
Eyelid edema | 21 (2) | 5 (1)
Conjunctivitis allergic | 19 (2) | 11 (2)
Ocular discomfort** | 18 (2) | 11 (2)
Ocular and conjunctival hyperemia | 17 (2) | 3 (1)
Lacrimation increased | 13 (1) | 10 (2)

*Includes “visual impairment”, “blurred vision” and “low vision acuity”

**Includes “foreign body sensation”, “ocular discomfort” and “abnormal sensation in the eye”

Hepatobiliary Adverse Reactions

More patients in the moxidectin arm experienced elevation in bilirubin above the upper limit of normal and elevation in transaminases > 5x upper limit of normal. Twenty-seven (2.8%) patients in the moxidectin arm and 3 (0.6%) patients in the ivermectin arm had hyperbilirubinemia. Most of the patients had single measurements of hyperbilirubinemia without concurrent elevation in transaminases.

Nine (1%) patients in the moxidectin arm and 2 (0.4%) patients in the ivermectin arm had elevation in ALT of more than 5x upper limit of normal; ten (1%) patients in the moxidectin arm and 3 (0.6%) patients in the ivermectin arm had elevation in AST to more than 5x upper limit of normal.

Laboratory Abnormalities

Laboratory abnormalities occurring in at least 1% of patients in Trial 1 are described in Table 4.

Table 4: Laboratory Abnormalities in at least 1% of Moxidectin-treated Patients
Parameter | MOXIDECTIN (N= 978) n (%) | Ivermectin (N= 494) n (%)
Hematology
Severe eosinophilia (> 5 x10^9/L) | 173 (18) | 111 (23)
Grade 3 lymphocytopenia (< 0.5 x10^9/L) | 220 (23) | 98 (20)
Grade 4 Neutrophils (< 0.5 x10^9/L) | 65 (7) | 46 (9)
Eosinopenia (< 0.045 x10^9/L) | 51 (5) | 21 (4)
Hepatobiliary
GGT (> 5x upper limit of normal) | 26 (3) | 16 (3)
Bilirubin (> 2x upper limit of normal) | 14 (1) | 2 (0.4)
AST (> 5x upper limit of normal) | 10 (1) | 3 (0.6)
ALT (> 5x upper limit of normal) | 9 (1) | 2 (0.4)

Clinical Trials Experience in Pediatric Patients (4 Years to Less than 18 Years of Age)

The safety of Moxidectin Tablets in pediatric patients is based on data from 2 studies, Trial 1 and Trial 3 (NCT01035619).

Pediatric Patients in Trial 1

Trial 1 included 53 pediatric patients aged 12 to less than 18 years with confirmed onchocerciasis who received a single dose of Moxidectin Tablets 8 mg. Pediatric patients with confirmed infection experienced efficacy-related adverse reactions (Mazzotti reactions) such as abdominal pain, tachycardia, pyrexia, rash, peripheral swelling, and lymph node pain at a prevalence and severity similar to infected adults. Overall, the safety profile relative to age was similar across pediatric and adult patients studied in Trial 1.

Pediatric Patients in Trial 3

Trial 3 was a single-arm, open-label, age-stratified, multi-cohort, safety and pharmacokinetic trial that evaluated 36 pediatric patients aged 4 to less than 18 years with unknown O. volvulus infection status from an onchocerciasis-endemic area in Ghana. Patients were stratified by age to receive a single dose of Moxidectin Tablets as follows: aged 12 to less than 18 years received 8 mg (N = 9), 8 to less than 12 years received 8 mg (N = 9) or 6 mg (N = 9), and 4 to less than 8 years received 4 mg (N = 9). Median weight was 34.8 kg (range: 30.8 to 55.5 kg) in patients 12 to less than 18 years of age, 25.1 kg (range: 19.4 to 36.8 kg) in patients 8 to less than 12 years, and 15.6 kg (range: 13.6 to 20.6 kg) in patients 4 to less than 8 years. A majority of patients were female (58%) and 100% were black. Mazzotti reactions were not seen in this population with unknown O. volvulus infection. The most common adverse reactions in these pediatric patients were abdominal pain and diarrhea, in 3/36 (8%) patients each. No new safety signals were noted in this pediatric patient population that were not already noted in Trial 1.

7 DRUG INTERACTIONS

7.1 Midazolam (CYP3A4 substrate)

In healthy subjects, concomitant administration of a single 8 mg oral dose of Moxidectin Tablets did not have an effect on the pharmacokinetics of midazolam [ see Clinical Pharmacology (12.3)]. Moxidectin can be co-administered with CYP3A4 substrates.

8 USE IN SPECIFIC POPULATIONS

8.1 Pregnancy

Risk Summary

Available data from clinical trials on the use of Moxidectin Tablets in pregnant women are insufficient to establish whether there is a moxidectin-associated risk for major birth defects and miscarriage .Moxidectin administered orally to pregnant rats during the period of organogenesis was not associated with significant embryo-fetal developmental effects at doses of approximately 15 times the recommended human dose based on body surface area (BSA) comparison. When moxidectin was dosed orally to pregnant rabbits during the period of organogenesis, no embryo-fetal developmental effects were observed at oral doses of moxidectin up to 24 times the recommended human dose based on BSA comparison (seeData).

Daily administration of moxidectin by oral gavage to maternal female rats during organogenesis and through lactation was associated with decreased survival, adverse clinical signs, and decreased body weights in first-generation offspring during the lactation period at a moxidectin dose less than 2-times the recommended human dose based on BSA comparison. Additional findings in first-generation offspring at the same dose included delays in pinna unfolding, eye opening, and vaginal opening. Other parameters, including reproduction and neurological development in first-generation offspring were not affected at any moxidectin dose (seeData).

The estimated background risk of major birth defects and miscarriage for the indicated population is unknown. All pregnancies have a background risk of birth defect, loss or other adverse outcomes. In the U.S. general population, the estimated background risk of major birth defects and miscarriage in clinically recognized pregnancies is 2% to 4% and 15% to 20%, respectively.

Data

Animal Data

In a rat embryo-fetal development study, daily oral administration of moxidectin at 12 mg/kg/day (approximately 15 times the recommended human dose of 8 mg based on BSA comparison) during Gestation Days (GDs) 6 to 15 significantly increased the fetal incidence, but not the litter incidence of cleft palate and the fetal and litter incidence of a skeletal variation, wavy ribs, at a maternally toxic dose. Mean maternal food consumption, body weights, and body weight gain were significantly decreased at moxidectin doses of 10 and 12 mg/kg/day compared to control values. The no observed adverse effect level (NOAEL) value for maternal and fetal toxicity was considered to be 5 and 10 mg/kg/day respectively (approximately 6 and 12 times, respectively, the recommended human dose based on BSA comparison). In the rabbit, daily oral administration of moxidectin at ≥ 5 mg/kg/day from GD 7 to GD 19 was not associated with fetal weight loss or malformations but resulted in significantly decreased maternal food consumption and body weight gains. The NOAEL values for maternal and fetal toxicity in the rabbit was 1 mg/kg/day and 10 mg/kg/day respectively (approximately 2 times and 24 times, respectively, the recommended human dose based on BSA comparison).

In a pre-postnatal study, moxidectin doses of 0.2 and 0.5 mg/kg/day were administered by oral gavage to maternal female rats from GD 6 throughout the lactation period until LD 21. A third dose group that received maternal doses of 1.5 mg/kg/day moxidectin (less than 2-times the recommended human dose based on BSA comparison) was divided into two cohorts with Cohort 1 receiving maternal doses from GD 6 until LD 10 and Cohort 2 receiving maternal doses from GD 6 until each individual animal littered, but not during the lactation period. First-generation offspring in Cohort 1 had adverse clinical signs (small body size, thin, weak, subdued/sluggish, pale, cold to touch, respiratory distress, blue coloration and/or no visible milk in stomach) and decreased survival and body weights during the lactation period. However, first-generation offspring in Cohort 2 did not experience adverse clinical signs, body weight loss, or reduced survival suggesting moxidectin in lactation milk was responsible for the adverse effects in offspring in Cohort 1. Additional findings included delays in pinna unfolding and eye opening in male and female offspring in both cohorts and delay of vaginal opening in female offspring in Cohort 2. No adverse effects were noted in offspring at a maternal dose of 0.5 mg/kg/day (approximately 0.6 times the recommended human dose based on BSA comparison). Reproductive performance based on mating and fertility indices and neurological development were not affected in male and female first-generation offspring at any of the administered moxidectin doses.

In another pre-postnatal study in rats, parental oral administration of dietary moxidectin prior to mating, through mating, gestation, and lactation did not produce adverse effects in first-generation or second-generation offspring at a maternal NOAEL dose of 0.824 mg/kg/day (approximately equivalent to the recommended human dose based on BSA comparison). However, at moxidectin doses ≥ 1.1 mg/kg/day (approximately equivalent to 1.3 times the recommended human dose based on BSA comparison), the survival and body weights of first-generation offspring were significantly decreased during the lactation period, and the number of live fetuses at birth was significantly decreased with a maternal moxidectin dose of 11 mg/kg/day (approximately equivalent to 13 times the recommended human dose based on BSA comparison). In this study, offspring were assessed for survival, body weights, and fertility, and developmental milestones were not assessed.

8.2 Lactation

Risk Summary

Moxidectin was detected in the milk of lactating women following a single 8 mg dose of Moxidectin Tablets (see Data). There are no data on the effects of Moxidectin Tablets on the breast-fed infant or milk production. In a pre-postnatal study in rats, oral gavage administration of moxidectin at a dose less than 2-times the recommended human dose based on BSA comparison during the lactation period resulted in adverse clinical signs, weight loss, and increased mortality in rat pups suggesting moxidectin in lactation milk was responsible for the adverse effects [see Use in Specific Populations (8.1), and Data].

Because of serious findings from the rat pre-postnatal study including weight loss and death, advise women that breastfeeding is not recommended at the time of treatment with Moxidectin Tablets and for 7 days after treatment.

Data

A pharmacokinetic study in twelve healthy adult lactating women who were 21 to 100 weeks post partum evaluated the concentrations of moxidectin in plasma and breast milk collected over a period of 28 days following a single 8 mg dose of Moxidectin Tablets. The mean (± SD) exposure ratio of moxidectin present in human breast milk to that of human plasma was approximately 1.77 mg(± 0.66) over a collection period of 28 days. The estimated mean (± SD) total infant dose, assuming the infants would consume all the breast milk collected during the study, was 0.056 mg (± 0.024 mg), which would be approximately 0.70% (± 0.30%) of the maternal dose. Relative infant dose was estimated to be 8.73% (± 0.024 mg). The effects of moxidectin or its metabolites on the breast-fed child or milk production were not evaluated.

8.4 Pediatric Use

The safety and effectiveness of Moxidectin Tablets for the treatment of onchocerciasis due to O. volvulus have been established in pediatric patients aged 4 years and older and weighing at least 13 kg. Use of Moxidectin Tablets for this indication is supported by evidence from adequate and well controlled studies in adult and pediatric patients aged 12 years and older with additional pharmacokinetics (PK) and safety data in pediatric patients aged 4 years and older [see Adverse Reactions (6.1), Clinical Pharmacology (12.3), and Clinical Studies (14)].

The safety and effectiveness of Moxidectin Tablets in pediatric patients younger than 4 years of age or weighing less than 13 kg has not been established.

8.5 Geriatric Use

Of the total number of patients included in Trial 1 that were treated with Moxidectin Tablets, 83 were aged 65 and over. No overall differences in safety or effectiveness were observed between these patients and younger patients, and other reported clinical experience has not identified differences in responses between the elderly and younger patients, but greater sensitivity of some older individuals cannot be ruled out [see Clinical Studies (14) and Clinical Pharmacology (12.3)].

8.6 Renal Impairment

No dose adjustment of Moxidectin Tablets is necessary for patients with mild (creatinine clearance (CrCL) 60 to 89 mL/min) to moderate (CrCL 30 to 59 mL/min) renal impairment. The safety of Moxidectin Tablets in patients with severe renal impairment (CrCL 15 to 29 mL/min) or end stage renal disease, is unknown [see Clinical Pharmacology (12.3)].

10 OVERDOSAGE

No specific antidote is available for overdose with Moxidectin Tablets. If overdose occurs, the patient should be monitored for evidence of toxicity. Treatment of overdose with Moxidectin Tablets consists of general supportive measures including monitoring of vital signs as well as observation of the clinical status of the patient. Supportive therapy, if indicated, should include parenteral fluids and electrolytes, respiratory support (oxygen and mechanical ventilation if necessary) and pressor agents if clinically significant hypotension is present.

11 DESCRIPTION

Moxidectin Tablets contain moxidectin, an anthelmintic drug and a macrocyclic lactone of the milbemycin class derived from the actinomycete Streptomyces cyanogriseus.

The chemical name of moxidectin is (2aE,4E,5'R,6R,6'S,8E,11R,13S,15S,17aR,20R,20aR,20bS)-6'-[(E)-1,3-dimethyl-1-butenyl]-5',6,6',7,10,11,14,15,17a,20,20a,20b-dodecahydro-20,20b-dihydroxy-5',6,8,19-tetramethylspiro[11,15-methano-2H,13H,17H-furo[4,3,2-pq][2,6]benzodioxacyclooctadecin-13,2'-[2H]pyran]-4',17(3'H)-dione 4'-(E)-(O-methyloxime). The structural formula is:

Figure 1: Moxidectin Structure

Moxidectin is a white or pale-yellow, amorphous powder. The empirical formula is C37H53NO8and the molecular weight is 639.82 Dalton. Moxidectin is readily soluble in organic solvents such as methylene chloride, diethyl ether, ethanol, acetonitrile, and ethyl acetate. It is only slightly soluble in water (0.51 mg/L) and the melting point range for moxidectin powder is 145°C to 154°C.

Moxidectin Tablets are for oral administration. Each tablet contains 2 mg of moxidectin. The tablets are uncoated and include the following inactive ingredients: colloidal silicon dioxide, croscarmellose sodium, lactose anhydrous, magnesium stearate, microcrystalline cellulose and sodium lauryl sulfate.

12 CLINICAL PHARMACOLOGY

12.1 Mechanism of Action

Moxidectin, a macrocyclic lactone, is an anthelmintic drug [see Microbiology (12.4)].

12.2 Pharmacodynamics

Cardiac Electrophysiology

At a dose 4.5 times the approved recommended dose, moxidectin does not prolong the QT interval to any clinically relevant extent.

12.3 Pharmacokinetics

The pharmacokinetic parameters of moxidectin following a single 8 mg oral dose of Moxidectin Tablets to healthy subjects and patients with onchocerciasis under fasted conditions are shown in Table 5. Mean moxidectin Cmaxand AUC increased approximately proportionally to dose over a dose range of 2 to 36 mg (0.25 to 4.5 times the approved recommended dose) in healthy subjects under fasted conditions.

Table 5: Mean (± SD) Pharmacokinetic Parameters of Moxidectin Following a Single 8 mg Oral Dose of Moxidectin Tablets to Healthy Subjects and Patients with Onchocerciasis Under Fasted Conditions
PK Parameter | Healthy Subjects (N =27) | Patients with Onchocerciasis (N = 31)
Cmax (ng/mL) | 58.9 ± 12.5 | 63.1 ± 20.0
Tmax*(hours) | 4 (2, 8) | 4 (1, 4)
AUCinf (ng•h/mL) | 3387 ± 1328 | 2738 ± 1606
Half-life (hours) | 784 ± 347 | 559 ± 525

Cmax= maximum plasma concentration; Tmax= time to reach Cmax; AUCinf= area under the plasma concentration-time curve from time 0 to infinity; * Median (range)

Absorption

Effect of Food

Moxidectin mean Cmaxand AUC increased on average by 34% and 39%, respectively, when administered with a standard high fat meal (900 calories, with a nutritional distribution of approximately 55% fat, 31% carbohydrates and 14% protein), compared to fasted conditions [see Dosage and Administration (2.1)].

Distribution

The apparent mean ± SD volume of distribution of moxidectin is 2421 ± 1658 L in patients with onchocerciasis. The plasma protein binding in humans is 99.92%.

Elimination

The mean terminal half-life of moxidectin in patients with onchocerciasis is 23.3 days (559 hours) following a single 8 mg dose of Moxidectin Tablets.

The apparent mean ± SD total clearance of moxidectin is approximately 3.50 ± 1.23 L/hour in patients with onchocerciasis.

Metabolism

The hepatic metabolism of moxidectin is minimal.

Excretion

Following administration of a single 8 mg oral dose of Moxidectin Tablets to healthy subjects, 2% of the dose is eliminated unchanged in the feces within the first 72 hours. Renal elimination of intact drug is negligible.

Specific Populations

In clinical studies, no clinically significant differences in the pharmacokinetics of moxidectin were observed based on age (18 to 60 years), sex, weight (42.7 to 107.2 kg), or renal impairment (creatinine clearance (CrCL) 47 to 89 mL/min, estimated by Cockcroft-Gault). The pharmacokinetics of moxidectin in patients with CrCL less than 47 mL/min is unknown. The pharmacokinetics of moxidectin in patients with hepatic impairment is unknown.

Patients with Renal Impairment

Based on a population pharmacokinetic analysis and negligible renal elimination of moxidectin, mild (creatinine clearance (CrCL), estimated by Cockcroft-Gault of 60 to 89 mL/min) and moderate (CrCL 30 to 59 mL/min) renal impairment is not likely to have an impact on the exposure of moxidectin. The effect of severe renal impairment (CrCL 15 to 29 mL/min) or of end-stage renal disease on the pharmacokinetics of moxidectin is unknown.

Pediatric Patients

A pharmacokinetic study was conducted in 36 pediatric patients aged 4 to 17 years with unknown O. volvulus infection status who were administered a single dose of moxidectin (4, 6, or 8 mg). Body weight was identified as a key covariate in the population pharmacokinetic analysis. The simulated mean pharmacokinetic parameters of moxidectin following a single 4, 6, and 8 mg oral dose of Moxidectin Tablets in a U.S. pediatric population weighing 13 kg to less than 15 kg, 15 kg to less than 30 kg, and 30 kg and greater, respectively, are shown in Table 6.

Table 6: Mean (CV%) Pharmacokinetic Parameters for Moxidectin Following a Single Oral Weight Based Dose of Moxidectin Tablets in Pediatric Patients

PK Parameter | Following 4 mg single dose in pediatric patients weighing 13 kg to less than 15 kg | Following 6 mg single dose in pediatric patients weighing 15 kg to less than 30 kg | Following 8 mg single dose in pediatric patients weighing 30 kg and greater
Cmax (ng/mL) | 80.9 (22.3%) | 90.9 (26.2%) | 65.2 (30.7%)
Tmax (hours) | 3.4 (34.1%) | 3.5 (34.7%) | 3.5 (34.1%)
AUCinf (ng•h/mL) | 2388.8 (42.2%) | 2840.2 (43.7%) | 2660.5 (41.9%)
Half-life (hours) | 299.0 (36.4%) | 338.2 (41.0%) | 545.8 (50.9%)

Cmax= maximum plasma concentration; Tmax= time to reach Cmax; AUCinf= area under the plasma concentration-time curve from time 0 to infinity; CV = coefficient of variation

Drug Interaction Studies

Clinical Studywith Midazolam (CYP3A4 substrate)

Co-administration of a single 8 mg dose of Moxidectin Tablets with a single oral 7.5 mg dose of midazolam (a sensitive CYP3A substrate) to healthy subjects (n = 37) did not affect the pharmacokinetics of midazolam or its major metabolite, 1-hydroxy midazolam.

In Vitro Studies

CYP Enzymes: Moxidectin is not a substrate or inhibitor of CYP enzymes.

Uridine 5'-diphospho-glucuronosyltransferases (UGTs): Moxidectin is not a UGT substrate.

Transporter Systems: Moxidectin is not a substrate of P-glycoprotein (P-gp) nor breast cancer resistance protein 1 (BCRP1).

12.4 Microbiology

Mechanism of Action

The mechanism by which moxidectin exhibits its effect against O. volvulusis not known. Studies with other nematodes suggest that moxidectin binds to glutamate-gated chloride channels (GluCl), gamma-aminobutyric acid (GABA) receptors and/or ATP-binding cassette (ABC) transporters. This leads to increased permeability, influx of chloride ions, hyperpolarization and muscle paralysis. Additionally, there is a reduction in motility of all stages of the parasite, excretion of immunomodulatory proteins, and the fertility of both male and female adult worms.

Antimicrobial activity

Moxidectin is active against the microfilariae of O. volvulus [see Clinical Studies (14)].

Studies suggest that moxidectin is not effective in killing the adult worms, however, it inhibits intra-uterine embryogenesis and release of microfilariae from the adult worms.

Resistance

Studies in vitroand in infected animals suggest a potential for development of resistance to moxidectin and cross-resistance with other macrocyclic lactones, such as ivermectin. However, the clinical relevance of these findings is not known.

The mechanism of resistance may be multifactorial that include alteration in the target GluCl, GABA receptors and/or ABC transporters.

13 NONCLINICAL TOXICOLOGY

13.1 Carcinogenesis, Mutagenesis, Impairment of Fertility

Carcinogenesis

Two-year carcinogenicity studies in mice and rats were conducted with moxidectin. Mice were administered a mean dietary dose of 8.7 mg/kg/day moxidectin which is approximately equivalent to 5 times the recommended human dose based on body surface area comparison. Rats were administered a mean dietary dose of 6.1 mg/kg/day moxidectin which is approximately equivalent to 7 times the recommended human dose based on body surface area comparison. There was no evidence of tumorigenicity in either study.

Mutagenesis

Moxidectin was shown to be negative for genotoxicity in a battery of in vitro assays including a bacterial mutagenicity assay, mouse lymphoma cell mutagenicity assay, unscheduled DNA synthesis assay, and a chromosome aberration assay, as well as in vivo in a micronucleus assay in mice and a chromosome aberration assay in rats.

Impairment of Fertility

In fertility evaluations, male and female mating and fertility indices were not inhibited by oral-dietary moxidectin doses of approximately 0.86 mg/kg/day which is approximately equivalent to the recommended human dose based on body surface area comparison.

13.2 Animal Toxicologyand/or Pharmacology

Moxidectin was associated with transient CNS-related clinical signs. In rats, a single oral dose of 20 mg/kg (equivalent to approximately 24 times the recommended human dose based on body surface area comparison) moxidectin was associated with piloerection, reduced arousal and body tone, abnormal gait, slowed breathing, and impaired righting reflex. In adult dogs, repeated oral doses of 1.6 mg/kg/day moxidectin (equivalent to approximately 7 times the recommended human dose based on body surface area comparison) was associated with lacrimation, languid appearance, tremors, slight salivation, and slight ataxia. Similar clinical signs that were largely resolved after 24 and 48 hours in juvenile (11-week-old) and adult (10-monthold) dogs, respectively, were observed after a single oral dose of 3 mg/kg moxidectin (respectively, approximately 34 and 50 times the maximum recommended human dose in patients with onchocerciasis based on plasma AUC comparison).

14 CLINICAL STUDIES

The assessment of the safety and efficacy of Moxidectin Tablets 8 mg in the treatment of onchocerciasis is based on data from two randomized, double-blind, active-controlled trials in patients with O. volvulusinfection, Trial 1 in 1472 patients (NCT 00790998), and Trial 2, a dose-ranging trial (NCT 00300768). Patients in the trials received a single oral dose of moxidectin or ivermectin, the active control medication.

Efficacy was assessed by skin microfilarial density (microfilariae/mg skin) from the mean of 4 skin snips per person per time point up to 18 months post-treatment.

Trial 1 recruited adult and pediatric patients ≥ 12 years with a body weight ≥ 30 kg and ≥ 10 microfilariae/mg skin. Mean (± SD) age was 42.5 (± 16.3) years, height 1.59 (± 0.09) meters, weight 51.6 (± 8.2) kg; 36.1% were female and 100% were black. Mean (± SD) pretreatment skin microfilarial density was 39.5 (± 30.7) microfilariae/mg skin, 69.6% had ≥ 20 microfilariae/mg skin and 39.7% had at least one ocular microfilaria.

Patients who were not previously exposed to ivermectin community directed treatment programs were recruited from the sub-Saharan African region (Democratic Republic of Congo, Liberia, and Ghana). Table 7 reports mean skin microfilarial density and the proportion of patients with undetectable skin microfilariae at Months 1, 6, and 12.

Table 7: Mean Microfilarial Density and Percentage of Undetectable Microfilariae in Skin of O. volvulus Adult and Pediatric Patients (12 Years of Age and Older) at Months 1, 6, and 12 in Trial 1
Endpoint | Moxidectin N = 977 | Ivermectin N = 495 | Difference (95% Confidence Interval)
1 month
Mean Microfilarial Densitya | 0.10 | 2.30 | -2.20 (-2.83, -1.58) p < 0.0001
% Undetectable Microfilariae b | 83.4% | 42.9% | 40.5% (35.7, 45.3) p < 0.0001
6 months
Mean Microfilarial Density a | 0.14 | 3.71 | -3.57(-4.11, -3.03) p < 0.0001
% Undetectable Microfilariae b | 91.0% | 11.5% | 79.6% (76.3, 82.9) p < 0.0001
12 months
Mean Microfilarial Densitya | 1.79 | 9.83 | -8.04 (-9.11, -6.98) p < 0.0001
% Undetectable Microfilariae b | 45.9% | 5.4% | 40.4% (36.7, 44.1) p < 0.0001

a Mean microfilarial density in skin is the average microfilarial density (microfilariae count/mg skin) over skin snips from four sites.

b Proportion of subjects undetectable (defined as a mean skin microfilariae density of zero across all 4 skin snips).

Additionally, safety and efficacy were assessed in a smaller single ascending dose trial (Trial 2, NCT 00300768) comparing 2 mg (n = 44), 4 mg (n = 45) (2 mg and 4 mg are not approved doses) and 8 mg (n = 38) single doses of moxidectin to ivermectin. Trial 2 was conducted in Ghana in adults aged ≥ 18 to ≤ 60 years with O. volvulusinfection. Analysis of the baseline-to-12-month change in skin microfilarial density for the proposed moxidectin 8 mg dose showed statistically significant superiority to ivermectin, p < 0.001.

16 HOW SUPPLIED/STORAGE AND HANDLING

Moxidectin Tablets containing 2 mg moxidectin are white to pale yellow uncoated oval-shaped tablets, debossed on one side with “AKKA”. Each high-density polyethylene bottle contains 500 tablets (NDC 71705-050-01), a silica gel desiccant and rayon coil.

Store below 30°C (86°F).

- Protect from light.
- Once open, the full contents of the container should be used within 24 hours and discard any unused content.

17 PATIENT COUNSELING INFORMATION

Signs and Symptoms Associated with Microfilarial Death

Advise patients that they are likely to have flu like symptoms including malaise, myalgia, headache, tachycardia, hypotension and pruritus, most commonly during the first week after treatment. [see Warnings and Precautions (5.1)].

Symptomatic Orthostatic Hypotension

Advise patients that if they feel dizzy, faint or light-headed after taking Moxidectin Tablets, they should lie down until the symptoms resolve. [see Warnings and Precautions (5.2)].

Absence of Macrofilarial Activity

Advise patients that treatment with Moxidectin Tablets does not kill adult O. volvulusand that follow up evaluation is usually required.

Edemaand Worseningof Onchodermatitis

Advise patients with hyper-reactive onchodermatitis that they may be more likely to experience severe adverse reactions. [see Warnings and Precautions (5.4)].

Encephalopathy in Loa loa Co-infected Patients

Advise patients to report any symptoms of encephalopathy to their healthcare provider. [see Warnings and Precautions (5.3)].

Lactation

Advise women that breastfeeding is not recommended at the time of treatment with Moxidectin Tablets and for 7 days after treatment. [see Use in Specific Populations (8.2)].

Manufactured for: Medicines Development for Global Health, Melbourne, Victoria, Australia

© 2025 Medicines Development for Global Health. All rights reserved.

PRINCIPAL DISPLAY PANEL

NDC 71705-050-01
moxidectin
tablets
2 mg
500 tablets
Rx Only